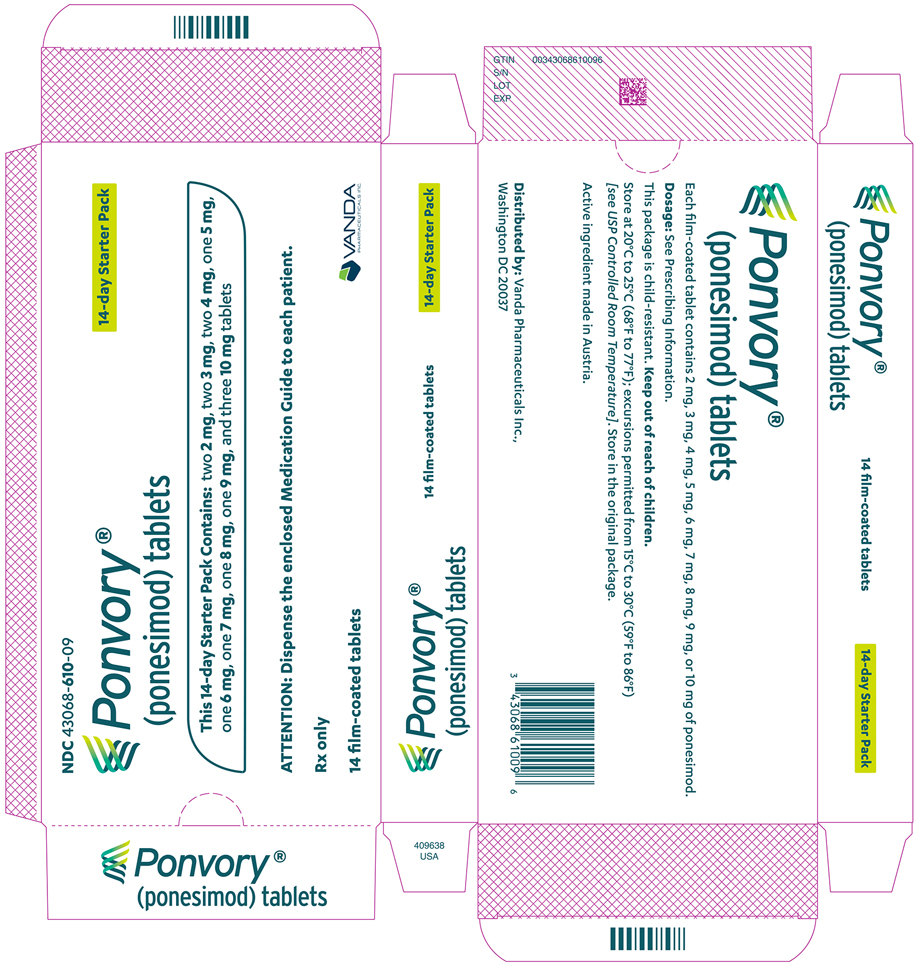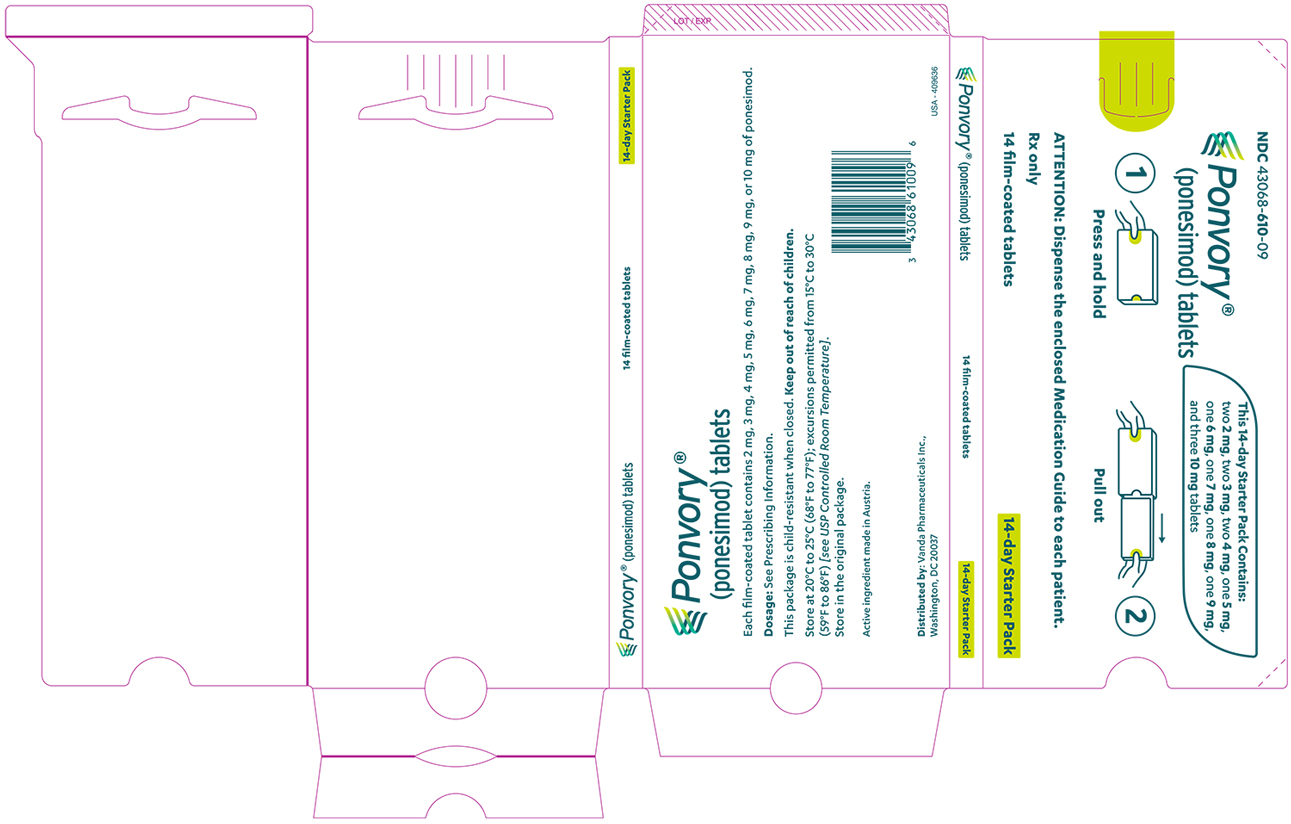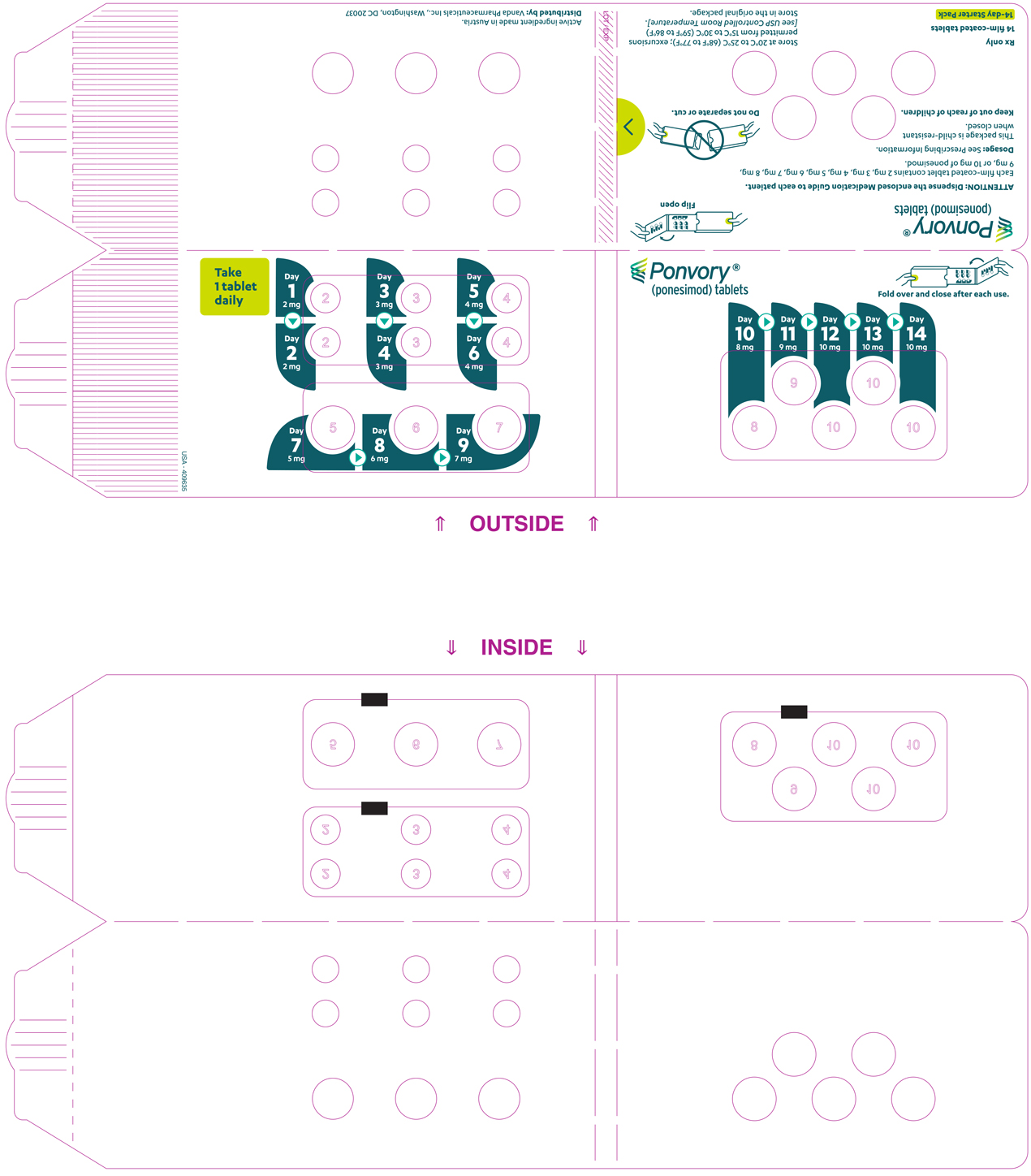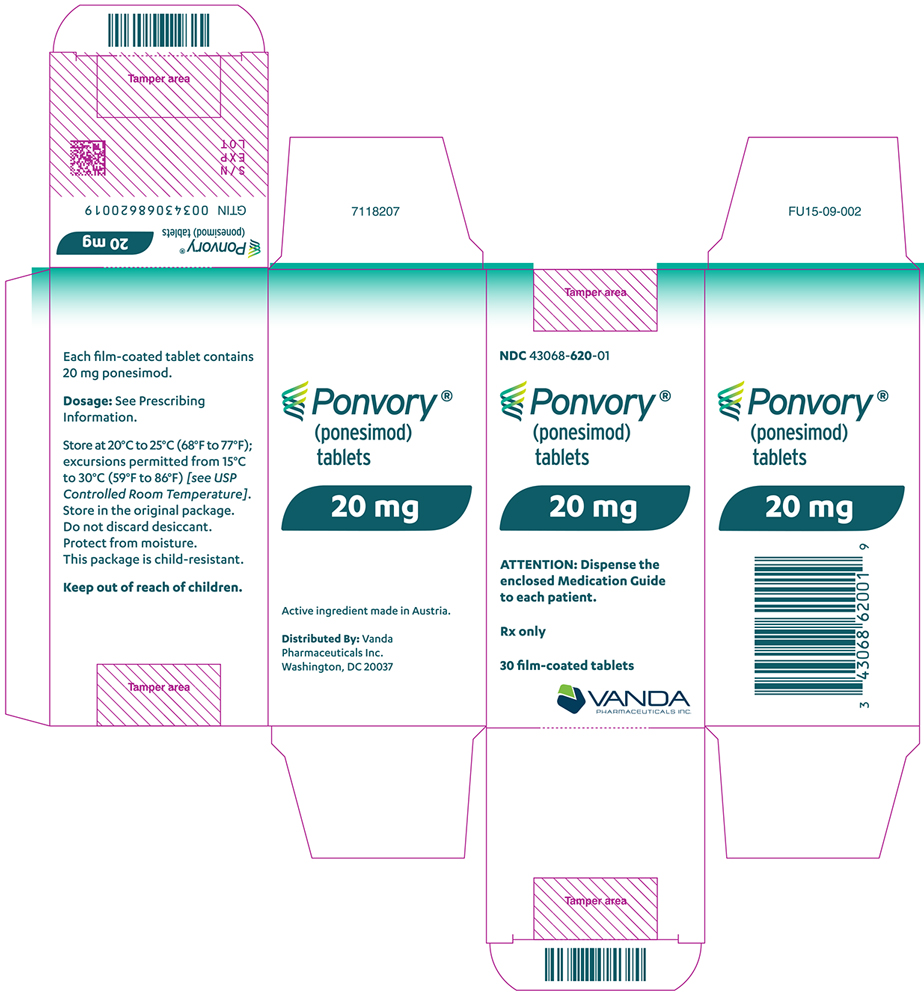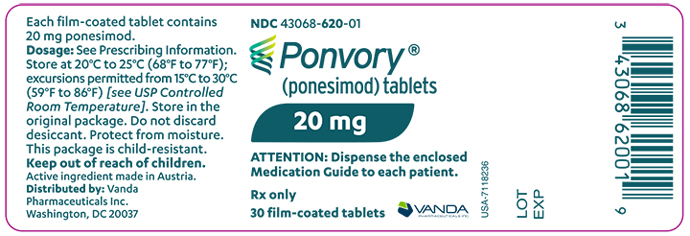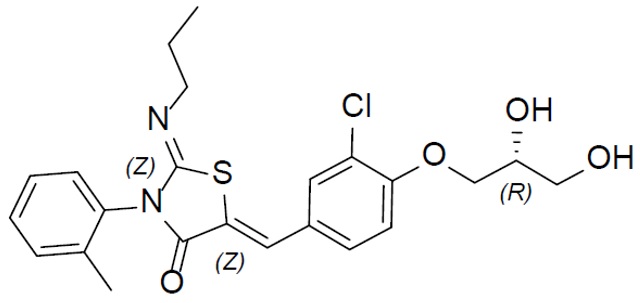 DRUG LABEL: PONVORY
NDC: 43068-620 | Form: TABLET, FILM COATED
Manufacturer: Vanda Pharmaceuticals Inc.
Category: prescription | Type: HUMAN PRESCRIPTION DRUG LABEL
Date: 20251204

ACTIVE INGREDIENTS: PONESIMOD 20 mg/1 1
INACTIVE INGREDIENTS: LACTOSE MONOHYDRATE; CROSCARMELLOSE SODIUM; MAGNESIUM STEARATE; MICROCRYSTALLINE CELLULOSE; POVIDONE K30; SILICON DIOXIDE; SODIUM LAURYL SULFATE; HYPROMELLOSE 2910 (15000 MPA.S); POLYETHYLENE GLYCOL, UNSPECIFIED; TITANIUM DIOXIDE; TRIACETIN; FERRIC OXIDE YELLOW

HIGHLIGHTS OF PRESCRIBING INFORMATION

These highlights do not include all the information needed to use PONVORY safely and effectively. See full prescribing information for PONVORY.
PONVORY® (ponesimod) tablets, for oral use
Initial U.S. Approval: 2021

RECENT MAJOR CHANGES

Dosage and Administration (2.1) | 06/2024
Warnings and Precautions (5.1, 5.11) | 08/2023
Warnings and Precautions (5.1, 5.6, 5.8) | 06/2024

1 INDICATIONS AND USAGE

PONVORY is a sphingosine 1-phosphate receptor modulator indicated for the treatment of relapsing forms of multiple sclerosis (MS), to include clinically isolated syndrome, relapsing-remitting disease, and active secondary progressive disease, in adults. (1)

2 DOSAGE AND ADMINISTRATION

- Assessments are required prior to initiating PONVORY (2.1)
- Titration is required for treatment initiation (2.2)
- The recommended maintenance dosage is 20 mg taken orally once daily (2.2)
- First-dose monitoring is recommended for patients with sinus bradycardia, first- or second-degree [Mobitz type I] atrioventricular (AV) block, or a history of myocardial infarction or heart failure (2.3)

3 DOSAGE FORMS AND STRENGTHS

Tablets: 2 mg, 3 mg, 4 mg, 5 mg, 6 mg, 7 mg, 8 mg, 9 mg, 10 mg, and 20 mg (3)

4 CONTRAINDICATIONS

- In the last 6 months, experienced myocardial infarction, unstable angina, stroke, transient ischemic attack (TIA), decompensated heart failure requiring hospitalization, or Class III/IV heart failure (4)
- Presence of Mobitz type II second-degree, third-degree AV block, sick sinus syndrome, or sino-atrial block, unless the patient has a functioning pacemaker (4)

5 WARNINGS AND PRECAUTIONS

- Infections: PONVORY may increase the risk of infections. Obtain a complete blood count (CBC) before initiating treatment. Monitor for infection during treatment and for 1-2 weeks after discontinuation. Do not start PONVORY in patients with active infection. (5.1)
- Bradyarrhythmia and Atrioventricular Conduction Delays: PONVORY may result in a transient decrease in heart rate; titration is required for treatment initiation. Check an electrocardiogram (ECG) to assess for preexisting cardiac conduction abnormalities before starting PONVORY. Consider cardiology consultation for conduction abnormalities or concomitant use with other drugs that decrease heart rate. (5.2, 7.2, 7.3)
- Respiratory Effects: May cause a decline in pulmonary function. Assess pulmonary function (e.g., spirometry) if clinically indicated. (5.3)
- Liver Injury: Discontinue if significant liver injury is confirmed. Obtain liver function tests before initiating PONVORY. (5.4)
- Increased Blood Pressure (BP): Monitor BP during treatment. (5.5)
- Cutaneous Malignancies: Skin examination prior to or shortly after the start of treatment and periodically is recommended. Suspicious skin lesions should be evaluated. (5.6)
- Fetal Risk: Women of childbearing potential should use effective contraception during and for 1 week after stopping PONVORY. (5.7)
- Macular Edema: Increases the risk of macular edema. Obtain a baseline evaluation of the fundus, including the macula, near the start of treatment with PONVORY. Conduct an evaluation of the fundus, including the macula, periodically while on therapy and any time there is a change in vision. Consider discontinuing PONVORY if macular edema develops. Diabetes mellitus and uveitis increase the risk. (5.8)

6 ADVERSE REACTIONS

Most common adverse reactions (incidence at least 10%) are upper respiratory tract infection, hepatic transaminase elevation, and hypertension. (6.1)

To report SUSPECTED ADVERSE REACTIONS, contact Vanda Pharmaceuticals, Inc. at 833-933-9331, FDA at 1-800-FDA-1088 or www.fda.gov/medwatch.

7 DRUG INTERACTIONS

Vaccines: Avoid live attenuated vaccines during and for up to 1-2 weeks after treatment with PONVORY. (7.4)

8 USE IN SPECIFIC POPULATIONS

Hepatic Impairment: PONVORY is not recommended in patients with moderate or severe hepatic impairment (Child-Pugh class B and C). (8.6)

FULL PRESCRIBING INFORMATION

1 INDICATIONS AND USAGE

PONVORY is indicated for the treatment of relapsing forms of multiple sclerosis (MS), to include clinically isolated syndrome, relapsing-remitting disease, and active secondary progressive disease, in adults.

2 DOSAGE AND ADMINISTRATION

2.1 Assessments Prior to First Dose of PONVORY

Before initiation of treatment with PONVORY, assess the following:

Cardiac Evaluation

Obtain an electrocardiogram (ECG) to determine whether preexisting conduction abnormalities are present. In patients with certain preexisting conditions, advice from a cardiologist should be sought and first-dose monitoring is recommended [see Dosage and Administration (2.3) and Warnings and Precautions (5.2)].

Complete Blood Count

Obtain a recent (i.e., within the last 6 months or after discontinuation of prior MS therapy) complete blood count (CBC), including lymphocyte count [see Warnings and Precautions (5.1)].

Determine whether patients are taking drugs that could slow heart rate or atrioventricular (AV) conduction [see Warnings and Precautions (5.2) and Drug Interactions (7.2, 7.3)].

Liver Function Tests

Obtain recent (i.e., within the last 6 months) transaminase and bilirubin levels [see Warnings and Precautions (5.4)].

Ophthalmic Evaluation

Obtain a baseline evaluation of the fundus, including the macula, near the start of treatment with PONVORY [see Warnings and Precautions (5.8)].

Skin Examination

Obtain a baseline skin examination prior to or shortly after initiation of PONVORY. If a suspicious skin lesion is observed, it should be promptly evaluated [see Warnings and Precautions (5.6)].

Current or Prior Medications with Immune System Effects

If patients are taking anti-neoplastic, immunosuppressive, or immune-modulating therapies, or if there is a history of prior use of these drugs, consider possible unintended additive immunosuppressive effects before initiating treatment with PONVORY [see Warnings and Precautions (5.1, 5.10) and Drug Interactions (7.1)].

Vaccinations

Test patients for antibodies to varicella zoster virus (VZV) before initiating PONVORY; VZV vaccination of antibody-negative patients is recommended prior to commencing treatment with PONVORY [see Warnings and Precautions (5.1)]. If live attenuated vaccine immunizations are required, administer at least 1 month prior to initiation of PONVORY.

2.2 Recommended Dosage

Maintenance Dosage

After dose titration is complete (see Treatment Initiation), the recommended maintenance dosage of PONVORY is 20 mg taken orally once daily starting on Day 15.

Administer PONVORY orally once daily. Swallow the tablet whole. PONVORY can be taken with or without food.

Treatment Initiation

A starter pack must be used for patients initiating treatment with PONVORY [see How Supplied/Storage and Handling (16.1)]. Initiate PONVORY treatment with a 14-day titration; start with one 2 mg tablet orally once daily and progress with the titration schedule as shown in Table 1 [see Warnings and Precautions (5.2)].

Table 1: Dose Titration Regimen

Titration Day | Daily Dose
Days 1 and 2 | 2 mg
Days 3 and 4 | 3 mg
Days 5 and 6 | 4 mg
Day 7 | 5 mg
Day 8 | 6 mg
Day 9 | 7 mg
Day 10 | 8 mg
Day 11 | 9 mg
Days 12, 13, and 14 | 10 mg

Maintenance | Daily Dose
Day 15 and thereafter | 20 mg

If dose titration is interrupted, missed dose instructions must be followed [see Dosage and Administration (2.4)].

2.3 First Dose Monitoring in Patients with Certain Preexisting Cardiac Conditions

Because initiation of PONVORY treatment results in a decrease in heart rate, first-dose 4-hour monitoring is recommended for patients with sinus bradycardia [heart rate less than 55 beats per minute (bpm)], first- or second-degree [Mobitz type I] AV block, or a history of myocardial infarction or heart failure occurring more than 6 months prior to treatment initiation and in stable condition [see Warnings and Precautions (5.2) and Clinical Pharmacology (12.2)].

First Dose 4-Hour Monitoring

Administer the first dose of PONVORY in a setting where resources to appropriately manage symptomatic bradycardia are available. Monitor patients for 4 hours after the first dose for signs and symptoms of bradycardia with a minimum of hourly pulse and blood pressure measurements. Obtain an ECG in these patients prior to dosing and at the end of the 4-hour observation period.

Additional Monitoring After 4-Hour Monitoring

If any of the following abnormalities are present after 4 hours (even in the absence of symptoms), continue monitoring until the abnormality resolves:

- The heart rate 4 hours post-dose is less than 45 bpm
- The heart rate 4 hours post-dose is at the lowest value post-dose, suggesting that the maximum pharmacodynamic effect on the heart may not have occurred
- The ECG 4 hours post-dose shows new onset second-degree or higher AV block

If post-dose symptomatic bradycardia, bradyarrhythmia, or conduction related symptoms occur, or if ECG 4 hours post-dose shows new onset second degree or higher AV block or QTc greater than or equal to 500 msec, initiate appropriate management, begin continuous ECG monitoring, and continue monitoring until the symptoms have resolved if no pharmacological treatment is required. If pharmacological treatment is required, continue monitoring overnight and repeat 4-hour monitoring after the second dose.

Advice from a cardiologist should be sought to determine the most appropriate monitoring strategy (which may include overnight monitoring) during treatment initiation, if treatment with PONVORY is considered in patients:

- With some preexisting heart and cerebrovascular conditions [see Warnings and Precautions (5.2)]
- With a prolonged QTc interval before dosing or during the 4-hour observation, or at additional risk for QT prolongation, or on concurrent therapy with QT prolonging drugs with a known risk of torsades de pointes [see Warnings and Precautions (5.2) and Drug Interactions (7.2)]
- Receiving concurrent therapy with drugs that slow heart rate or AV conduction [see Drug Interactions (7.2, 7.3)]

2.4 Reinitiation of PONVORY After Treatment Interruption

Interruption during treatment, especially during titration, is not recommended; however:

- If fewer than 4 consecutive doses are missed:
  - during titration: resume treatment with the first missed titration dose and resume the titration schedule at that dose and titration day.
  - during maintenance: resume treatment with the maintenance dosage.
- If 4 or more consecutive doses are missed during titration or maintenance:
  - treatment should be reinitiated with Day 1 of the titration regimen (new starter pack).

If treatment needs to be reinitiated with Day 1 of the titration regimen (new starter pack), complete first-dose monitoring in patients for whom it is recommended [see Dosage and Administration (2.3)].

3 DOSAGE FORMS AND STRENGTHS

PONVORY is available as round, biconvex, film-coated tablets for oral use. PONVORY contains ponesimod in the following dosage strengths (see Table 2):

Table 2: Dosage Form and Strengths for PONVORY

Tablet Strength | Tablet Color | Tablet Size | Tablet Debossing
2 mg | White | 5.0 mm | "2" on one side and an arch on the other side.
3 mg | Red | 5.0 mm | "3" on one side and an arch on the other side.
4 mg | Purple | 5.0 mm | "4" on one side and an arch on the other side.
5 mg | Green | 8.6 mm | "5" on one side and an arch and an "A" on the other side.
6 mg | White | 8.6 mm | "6" on one side and an arch and an "A" on the other side.
7 mg | Red | 8.6 mm | "7" on one side and an arch and an "A" on the other side.
8 mg | Purple | 8.6 mm | "8" on one side and an arch and an "A" on the other side.
9 mg | Brown | 8.6 mm | "9" on one side and an arch and an "A" on the other side.
10 mg | Orange | 8.6 mm | "10" on one side and an arch and an "A" on the other side.
20 mg | Yellow | 8.6 mm | "20" on one side and an arch and an "A" on the other side.

4 CONTRAINDICATIONS

PONVORY is contraindicated in patients who:

- In the last 6 months, have experienced myocardial infarction, unstable angina, stroke, transient ischemic attack (TIA), decompensated heart failure requiring hospitalization, or Class III or IV heart failure [see Warnings and Precautions (5.2)]
- Have presence of Mobitz type II second-degree, third-degree AV block, sick sinus syndrome, or sino-atrial block, unless patient has a functioning pacemaker [see Warnings and Precautions (5.2)]

5 WARNINGS AND PRECAUTIONS

5.1 Infections

Risk of Infections

PONVORY causes a dose-dependent reduction in peripheral lymphocyte count to 30-40% of baseline values because of reversible sequestration of lymphocytes in lymphoid tissues [see Clinical Pharmacology (12.2)]. PONVORY may therefore increase the susceptibility to infections. Life-threatening and rare fatal infections have been reported in association with other sphingosine 1-phosphate (S1P) receptor modulators.

In Study 1 [see Clinical Studies (14)], the overall rate of infections was comparable between the PONVORY-treated patients and those receiving teriflunomide 14 mg (54.2% vs 52.1%, respectively). PONVORY increased the risk of upper respiratory tract infections. Serious or severe infections occurred in 1.6% of PONVORY-treated patients compared to 0.9% of patients receiving teriflunomide 14 mg.

Before initiating treatment with PONVORY, results from a recent (i.e., within 6 months or after discontinuation of prior therapy) complete blood count including lymphocyte count should be reviewed.

Initiation of treatment with PONVORY should be delayed in patients with active infection until resolution. Lymphocyte counts returned to the normal range in 90% of patients within 1 week of stopping therapy in modeling studies [see Clinical Pharmacology (12.2)]. In Study 1, peripheral lymphocyte counts returned to normal range within 2 weeks after discontinuation of PONVORY, which was the first timepoint evaluated. Because residual pharmacodynamic effects, such as lowering effects on peripheral lymphocyte count, may persist for 1 to 2 weeks after discontinuation of PONVORY, vigilance for infection should be continued for 1 to 2 weeks after PONVORY is discontinued [see Warnings and Precautions (5.12)].

In Study 1, the proportion of patients who experienced lymphocyte counts less than 0.2x10^9/L was 3.2%. Effective diagnostic and therapeutic strategies should be employed in patients with symptoms of infection while on therapy. Consider interruption of treatment with PONVORY if a patient develops a serious infection.

Herpes Viral Infections

Cases of herpes viral infection have been reported in the development program of PONVORY; herpes simplex encephalitis and varicella zoster meningitis have been reported with other S1P receptor modulators.

In Study 1, the rate of herpetic infections was 4.8% for both PONVORY-treated patients and those receiving teriflunomide 14 mg. Patients without a healthcare professional confirmed history of varicella (chickenpox) or without documentation of a full course of vaccination against VZV should be tested for antibodies to VZV before initiating PONVORY (see Vaccinations).

Cryptococcal Infections

Cases of fatal cryptococcal meningitis (CM) and disseminated cryptococcal infections have been reported with other S1P receptor modulators. Physicians should be vigilant for clinical symptoms or signs of CM. Patients with symptoms or signs consistent with a cryptococcal infection should undergo prompt diagnostic evaluation and treatment. PONVORY treatment should be suspended until a cryptococcal infection has been excluded. If CM is diagnosed, appropriate treatment should be initiated.

Progressive Multifocal Leukoencephalopathy

Progressive multifocal leukoencephalopathy (PML) is an opportunistic viral infection of the brain caused by the JC virus (JCV) that typically only occurs in patients who are immunocompromised, and that usually leads to death or severe disability. Typical symptoms associated with PML are diverse, progress over days to weeks, and include progressive weakness on one side of the body or clumsiness of limbs, disturbance of vision, and changes in thinking, memory, and orientation leading to confusion and personality changes.

PML has been reported in patients treated with S1P receptor modulators and other multiple sclerosis (MS) therapies and has been associated with some risk factors (e.g., immunocompromised patients, polytherapy with immunosuppressants, duration of use). Longer treatment duration increases the risk of PML in patients treated with S1P receptor modulators, and the majority of PML cases have occurred in patients treated with S1P receptor modulators for at least 18 months. Physicians should be vigilant for clinical symptoms or magnetic resonance imaging (MRI) findings that may be suggestive of PML. MRI findings may be apparent before clinical signs or symptoms. If PML is suspected, treatment with PONVORY should be suspended until PML has been excluded.

If PML is confirmed, treatment with PONVORY should be discontinued.

Immune reconstitution inflammatory syndrome (IRIS) has been reported in patients treated with S1P receptor modulators who developed PML and subsequently discontinued treatment. IRIS presents as a clinical decline in the patient’s condition that may be rapid, can lead to serious neurological complications or death, and is often associated with characteristic changes on MRI. The time to onset of IRIS in patients with PML was generally within a few months after S1P receptor modulator discontinuation. Monitoring for development of IRIS and appropriate treatment of the associated inflammation should be undertaken.

Prior and Concomitant Treatment with Anti-neoplastic, Immune-Modulating, or Immunosuppressive Therapies

Anti-neoplastic, immune-modulating, or immunosuppressive therapies (including corticosteroids) should be coadministered with caution because of the risk of additive immune system effects [see Drug Interactions (7.1)].

Vaccinations

Patients without a healthcare professional confirmed history of chickenpox or without documentation of a full course of vaccination against VZV should be tested for antibodies to VZV before initiating PONVORY treatment. A full course of vaccination for antibody-negative patients with varicella vaccine is recommended prior to commencing treatment with PONVORY, following which initiation of treatment with PONVORY should be postponed for 4 weeks to allow the full effect of vaccination to occur.

No clinical data are available on the efficacy and safety of vaccinations in patients taking PONVORY. Vaccinations may be less effective if administered during PONVORY treatment.

If live attenuated vaccine immunizations are required, administer at least 1 month prior to initiation of PONVORY. Avoid the use of live attenuated vaccines during and for 1 to 2 weeks after treatment with PONVORY.

5.2 Bradyarrhythmia and Atrioventricular Conduction Delays

Since initiation of PONVORY treatment results in a transient decrease in heart rate and AV conduction delays, an up-titration scheme must be used to reach the maintenance dosage of PONVORY (20 mg) [see Dosage and Administration (2.2) and Clinical Pharmacology (12.2)].

Study 1 did not include patients who had:

- A resting heart rate less than 50 beats per minute (bpm) on baseline electrocardiogram
- Myocardial infarction or unstable ischemic heart disease in the last 6 months
- Cardiac failure (New York Heart Association class III-IV) or presence of any severe cardiac disease
- Cardiac conduction or rhythm disorders (including sino-atrial heart block, symptomatic bradycardia, atrial flutter or atrial fibrillation, ventricular arrhythmia, cardiac arrest) either in history or observed at screening
- Mobitz Type II second degree AV block or higher-grade AV block observed at screening
- QTcF interval greater than 470 ms (females) and greater than 450 ms (males) observed at screening
- History of syncope associated with cardiac disorders
- Uncontrolled systemic arterial hypertension

Reduction in Heart Rate

Initiation of PONVORY may result in a transient decrease in heart rate. In Study 1, bradycardia at treatment initiation and sinus bradycardia on ECG (defined as heart rate less than 50 bpm) occurred in 5.8% of PONVORY-treated patients compared to 1.6% of patients receiving teriflunomide 14 mg. After the first titration dose of PONVORY, the decrease in heart rate typically begins within an hour and reaches its nadir within 2-4 hours. The heart rate typically recovers to baseline levels 4-5 hours after administration. The mean decrease in heart rate on Day 1 of dosing was 6 bpm. With up-titration after Day 1, the post-dose decrease in heart rate is less pronounced. Bradycardia resolved in all patients in Study 1 without intervention and did not require discontinuation of PONVORY treatment. On Day 1, 3 patients treated with PONVORY had asymptomatic post-dose heart rate below or equal to 40 bpm; all 3 patients had baseline heart rates below 55 bpm.

Atrioventricular Conduction Delays

Initiation of PONVORY treatment has been associated with transient atrioventricular conduction delays that follow a similar temporal pattern as the observed decrease in heart rate during dose titration. In Study 1, the AV conduction delays manifested as first-degree AV block (prolonged PR interval on ECG), which occurred in 3.4% of PONVORY-treated patients and in 1.2% of patients receiving teriflunomide 14 mg. The conduction abnormalities typically were transient, asymptomatic, resolved within 24 hours, resolved without intervention, and did not require discontinuation of PONVORY treatment. In Study 1, second- and third-degree AV blocks were not reported in patients treated with PONVORY.

If treatment with PONVORY is considered, advice from a cardiologist should be sought for individuals:

- With significant QT prolongation (QTc greater than 500 msec)
- With atrial flutter/fibrillation or arrhythmia treated with Class Ia or Class III anti-arrhythmic drugs [see Drug Interactions (7.2)]
- With unstable ischemic heart disease, cardiac decompensated failure occurring more than 6 months prior to treatment initiation, history of cardiac arrest, cerebrovascular disease (TIA, stroke occurring more than 6 months prior to treatment initiation), or uncontrolled hypertension
- With a history of Mobitz Type II second degree AV block or higher-grade AV block, sick- sinus syndrome, or sino-atrial heart block [see Contraindications (4)]

Treatment Initiation Recommendations

- Obtain an ECG in all patients to determine whether preexisting conduction abnormalities are present.
- In all patients, a dose titration is recommended for initiation of PONVORY treatment to help reduce cardiac effects [see Dosage and Administration (2.2)].
- In patients with sinus bradycardia, first-or second-degree [Mobitz type I] AV block, or a history of myocardial infarction or heart failure with onset more than 6 months prior to initiation, first-dose monitoring is recommended [see Dosage and Administration (2.1, 2.3)].
- PONVORY is not recommended in patients with a history of cardiac arrest, cerebrovascular disease (e.g., TIA, stroke occurring more than 6 months prior to treatment initiation), uncontrolled hypertension, or severe untreated sleep apnea, since significant bradycardia may be poorly tolerated in these patients. If treatment is considered, advice from a cardiologist should be sought prior to initiation of treatment in order to determine the most appropriate monitoring strategy.
- Use of PONVORY in patients with a history of recurrent syncope or symptomatic bradycardia should be based on an overall benefit-risk assessment. If treatment is considered, advice from a cardiologist should be sought prior to initiation of treatment in order to determine the most appropriate monitoring.
- Experience with PONVORY is limited in patients receiving concurrent therapy with drugs that decrease heart rate (e.g., beta-blockers, non-dihydropyridine calcium channel blockers - diltiazem and verapamil, and other drugs that may decrease heart rate such as digoxin). Concomitant use of these drugs during PONVORY initiation may be associated with severe bradycardia and heart block. If treatment is considered, advice from a cardiologist should be sought prior to initiation of treatment in order to determine the most appropriate monitoring.
  - For patients receiving a stable dose of a beta-blocker, the resting heart rate should be considered before introducing PONVORY treatment. If the resting heart rate is greater than 55 bpm under chronic beta-blocker treatment, PONVORY can be introduced. If resting heart rate is less than or equal to 55 bpm, beta-blocker treatment should be interrupted until the baseline heart rate is greater than 55 bpm. Treatment with PONVORY can then be initiated and treatment with a beta-blocker can be reinitiated after PONVORY has been up-titrated to the target maintenance dosage [see Drug Interactions (7.3)].
  - For patients taking other drugs that decrease heart rate, treatment with PONVORY should generally not be initiated without consultation from a cardiologist because of the potential additive effect on heart rate [see Dosage and Administration (2.3) and Drug Interactions (7.2)].

Missed Dose During Treatment Initiation or Maintenance Treatment

If 4 or more consecutive daily doses are missed during treatment initiation or maintenance treatment, reinitiate Day 1 of the dose titration (new starter pack) and follow first-dose monitoring recommendations [see Dosage and Administration (2.4)].

5.3 Respiratory Effects

Dose-dependent reductions in forced expiratory volume over 1 second (FEV1) and reductions in diffusion lung capacity for carbon monoxide (DLCO) were observed in PONVORY-treated patients mostly occurring in the first month after treatment initiation. In Study 1, the reduction from baseline in percent predicted FEV1 at 2 years was 8.3% in PONVORY-treated patients compared to 4.4% in patients receiving teriflunomide 14 mg. In Study 1, 7 patients discontinued PONVORY because of pulmonary adverse events. There is insufficient information to determine the reversibility of the decrease in FEV1 or FVC after treatment discontinuation. PONVORY should be used with caution in patients with severe respiratory disease (i.e., pulmonary fibrosis, asthma, and chronic obstructive pulmonary disease). Spirometric evaluation of respiratory function should be performed during therapy with PONVORY if clinically indicated.

5.4 Liver Injury

Elevations of transaminases may occur in PONVORY-treated patients.

Obtain transaminase and bilirubin levels, if not recently available (i.e., within last 6 months) before initiation of PONVORY.

In Study 1, elevations of ALT to 5-fold the upper limit of normal (ULN) or greater occurred in 4.6% of patients treated with PONVORY compared to 2.5% of patients who received teriflunomide 14 mg. Elevation of ALT to 3-fold the ULN or greater occurred in 17.3% of patients treated with PONVORY and 8.3% of patients treated with teriflunomide 14 mg. The median time to an elevation of 3-fold the ULN was 3 months. The majority (89%) of patients with ALT increases 3-fold or greater the ULN continued treatment with PONVORY with values returning to less than three times the ULN within approximately 2-4 weeks.

In Study 1, the discontinuation rate because of elevations in hepatic enzymes was 2.3% of patients treated with PONVORY and 1.9% of patients who received teriflunomide 14 mg.

Patients who develop symptoms suggestive of hepatic dysfunction, such as unexplained nausea, vomiting, abdominal pain, fatigue, anorexia, rash with eosinophilia, or jaundice and/or dark urine during treatment, should have hepatic enzymes checked. PONVORY should be discontinued if significant liver injury is confirmed.

No dosage adjustment is necessary in patients with mild hepatic impairment (Child-Pugh class A). PONVORY is not recommended in patients with moderate or severe hepatic impairment (Child- Pugh class B and C, respectively) [see Use in Specific Populations (8.6) and Clinical Pharmacology (12.3)].

5.5 Increased Blood Pressure

In Study 1, PONVORY-treated patients had an average increase of 2.9 mm Hg in systolic blood pressure and 2.8 mm Hg in diastolic blood pressure compared to 2.8 mm Hg and 3.1 mm Hg in patients receiving teriflunomide 14 mg, respectively. An increase in blood pressure with PONVORY was first detected after approximately 1 month of treatment initiation and persisted with continued treatment. Hypertensive events were reported as an adverse reaction in 10.1% of PONVORY-treated patients and in 9.0% of patients receiving teriflunomide 14 mg. One patient treated with PONVORY experienced a hypertensive crisis but had evidence of longstanding hypertensive heart disease. Blood pressure should be monitored during treatment with PONVORY and managed appropriately.

5.6 Cutaneous Malignancies

The risk of cutaneous malignancies (including basal cell carcinoma (BCC), squamous cell carcinoma (SCC), and melanoma) is increased in patients treated with S1P receptor modulators. Use of PONVORY has been associated with an increased risk of BCC.

In Study 1, the incidence of basal cell carcinoma was 0.4% in PONVORY-treated patients compared to 0.2% in patients receiving teriflunomide 14 mg [see Adverse Reactions (6.1)]. Cases of other cutaneous malignancies, including melanoma and squamous cell carcinoma, have also been reported in patients treated with PONVORY and in patients treated with other S1P receptor modulators. Kaposi’s sarcoma and Merkel cell carcinoma have also been reported in patients treated with S1P receptor modulators in the postmarketing setting.

Skin examinations are recommended prior to or shortly after the start of treatment and periodically thereafter for all patients, particularly those with risk factors for skin cancer. Providers and patients are advised to monitor for suspicious skin lesions. If a suspicious skin lesion is observed, it should be promptly evaluated. As usual for patients with increased risk for skin cancer, exposure to sunlight and ultraviolet light should be limited by wearing protective clothing and using a sunscreen with a high protection factor. Concomitant phototherapy with UV-B radiation or PUVA photochemotherapy is not recommended in patients taking PONVORY.

5.7 Fetal Risk

Based on animal studies, PONVORY may cause fetal harm [see Use in Specific Populations (8.1, 8.3)]. Because it takes approximately 1 week to eliminate PONVORY from the body, women of childbearing potential should use effective contraception to avoid pregnancy during and for 1 week after stopping PONVORY treatment.

5.8 Macular Edema

S1P receptor modulators, including PONVORY, have been associated with an increased risk of macular edema. Obtain a baseline evaluation of the fundus, including the macula, near the start of treatment with PONVORY. Perform an examination of the fundus, including the macula, periodically while on therapy and any time there is a change in vision.

In Study 1, macular edema was reported in 1.1% of PONVORY-treated patients compared to none of the patients receiving teriflunomide 14 mg.

Continuation of PONVORY therapy in patients with macular edema has not been evaluated. Macular edema over an extended period of time (i.e., 6 months) can lead to permanent visual loss. Consider discontinuing PONVORY if macular edema develops; this decision should include an assessment of the potential benefits and risks for the individual patient. The risk of recurrence after rechallenge has not been evaluated.

Macular Edema in Patients with a History of Uveitis or Diabetes Mellitus

Patients with a history of uveitis and patients with diabetes mellitus are at increased risk of macular edema during therapy with S1P receptor modulators, including PONVORY.

5.9 Posterior Reversible Encephalopathy Syndrome

Rare cases of posterior reversible encephalopathy syndrome (PRES) have been reported in patients receiving a S1P receptor modulator. Such events have not been reported for PONVORY-treated patients in the development program. However, should a PONVORY-treated patient develop any unexpected neurological or psychiatric symptoms/signs (e.g., cognitive deficits, behavioral changes, cortical visual disturbances, or any other neurological cortical symptoms/signs), any symptom/sign suggestive of an increase of intracranial pressure, or accelerated neurological deterioration, the physician should promptly schedule a complete physical and neurological examination and should consider an MRI. Symptoms of PRES are usually reversible but may evolve into ischemic stroke or cerebral hemorrhage. Delay in diagnosis and treatment may lead to permanent neurological sequelae. If PRES is suspected, PONVORY should be discontinued.

5.10 Unintended Additive Immunosuppressive Effects From Prior Treatment With Immunosuppressive or Immune-Modulating Therapies

When switching from drugs with prolonged immune effects, the half-life and mode of action of these drugs must be considered in order to avoid unintended additive effects on the immune system while at the same time minimizing risk of disease reactivation, when initiating PONVORY.

Initiating treatment with PONVORY after treatment with alemtuzumab is not recommended.

5.11 Severe Increase in Disability After Stopping PONVORY

Severe exacerbation of disease, including disease rebound, has been rarely reported after discontinuation of a S1P receptor modulator. The possibility of severe exacerbation of disease should be considered after stopping PONVORY treatment. Patients should be observed for a severe increase in disability upon PONVORY discontinuation and appropriate treatment should be instituted, as required.

After stopping PONVORY in the setting of PML, monitor for development of immune reconstitution inflammatory syndrome (PML-IRIS) [see Warnings and Precautions (5.1)].

5.12 Immune System Effects After Stopping PONVORY

After stopping PONVORY therapy, ponesimod remains in the blood for up to 1 week. Starting other therapies during this interval will result in concomitant exposure to ponesimod. Lymphocyte counts returned to the normal range in 90% of patients within 1 week of stopping PONVORY therapy in modeling studies [see Clinical Pharmacology (12.2)]. However, residual pharmacodynamics effects, such as lowering effects on peripheral lymphocyte count, may persist for 1 to 2 weeks after the last dose. Use of immunosuppressants within this period may lead to an additive effect on the immune system, and therefore caution should be applied 1 to 2 weeks after the last dose of PONVORY [see Drug Interactions (7.1)].

6 ADVERSE REACTIONS

The following serious adverse reactions are described elsewhere in labeling:

- Infections [see Warnings and Precautions (5.1)]
- Bradyarrhythmia and Atrioventricular Conduction Delays [see Warnings and Precautions (5.2)]
- Respiratory Effects [see Warnings and Precautions (5.3)]
- Liver Injury [see Warnings and Precautions (5.4)]
- Increased Blood Pressure [see Warnings and Precautions (5.5)]
- Cutaneous Malignancies [see Warnings and Precautions (5.6)]
- Fetal Risk [see Warnings and Precautions (5.7)]
- Macular Edema [see Warnings and Precautions (5.8)]
- Posterior Reversible Encephalopathy Syndrome [see Warnings and Precautions (5.9)]
- Unintended Additive Immunosuppressive Effects From Prior Treatment With Immunosuppressive or Immune-Modulating Therapies [see Warnings and Precautions (5.10)]
- Severe Increase in Disability After Stopping PONVORY [see Warnings and Precautions (5.11)]
- Immune System Effects After Stopping PONVORY [see Warnings and Precautions (5.12)]

6.1 Clinical Trials Experience

Because clinical trials are conducted under widely varying conditions, adverse reaction rates observed in the clinical trials of a drug cannot be directly compared to rates in the clinical trials of another drug and may not reflect the rates observed in practice.

A total of 1438 MS patients have received PONVORY at doses of at least 2 mg daily. These patients were included in Study 1 (2-year active-controlled versus teriflunomide 14 mg) [see Clinical Studies (14)] and in a Phase 2 (6-month placebo-controlled) study in patients with MS and the uncontrolled extension studies.

In Study 1, 82% of PONVORY-treated patients completed 2 years of study treatment, compared to 82.2% of patients receiving teriflunomide 14 mg. Adverse events led to discontinuation of treatment in 8.7% of PONVORY-treated patients, compared to 6% of patients receiving teriflunomide 14 mg. The most common adverse reactions (incidence at least 10%) in PONVORY-treated patients in Study 1 were upper respiratory tract infection, hepatic transaminase elevation, and hypertension. Table 3 lists adverse reactions that occurred in at least 2% of PONVORY-treated patients and at a higher rate than in patients receiving teriflunomide 14 mg.

Table 3: Adverse Reactions Reported in Study 1 Occurring in at Least 2% of PONVORY-Treated Patients and at a Higher Rate Than in Patients Receiving Teriflunomide 14 mg
Adverse Reaction | PONVORY N=565 (%) | Teriflunomide 14 mg N=566 (%)
Upper respiratory infectiona | 37 | 34
Hepatic transaminase elevationb | 23 | 12
Hypertensionc | 10 | 9
Urinary tract infection | 6 | 5
Dyspnea | 5 | 1
Dizziness | 5 | 3
Cough | 4 | 2
Pain in extremity | 4 | 3
Somnolence | 3 | 2
Pyrexia | 2 | 1
C-reactive protein increased | 2 | 1
Hypercholesterolemia | 2 | 1
Vertigo | 2 | 1
aIncludes the following terms: nasopharyngitis, upper respiratory tract infection, pharyngitis, respiratory tract infection, bronchitis, respiratory tract infection viral, viral upper respiratory tract infection, tracheitis, and laryngitis.
bIncludes the following terms: alanine aminotransferase increased, aspartate aminotransferase increased, hepatic enzyme increased, and transaminases increased.
cIncludes the following terms: hypertension, hypertensive crisis, blood pressure increased, blood pressure systolic increased, and blood pressure diastolic increased.

In Study 1, the following adverse reactions occurred in less than 2% of PONVORY-treated patients, but at a rate at least 1% higher than in patients receiving teriflunomide 14 mg: viral infection, herpes zoster, hyperkalemia, lymphopenia [see Warnings and Precautions (5.1), and macular edema [see Warnings and Precautions (5.8)].

Adverse reactions in patients treated with PONVORY in an additional 6-month placebo-controlled study were generally similar to those in Study 1. The following additional adverse reactions occurred in at least 2% of PONVORY 20 mg-treated patients and at a higher rate than in patients receiving placebo (but did not meet the reporting rate criteria for inclusion in Study 1): rhinitis, fatigue, chest discomfort, peripheral edema, joint swelling, blood cholesterol increased, migraine, insomnia, depression, dyspepsia, dry mouth, bradycardia, back pain, and sinusitis.

Additionally, in uncontrolled extension trials, the adverse reaction of pneumonia was reported.

Seizures

In Study 1, cases of seizures were reported in 1.4% of PONVORY-treated patients, compared to 0.2% in patients receiving teriflunomide 14 mg. It is not known whether these events were related to the effects of MS, to PONVORY, or to a combination of both.

Respiratory Effects

In Study 1, dose-dependent reductions in FEV1 were observed in patients treated with PONVORY [see Warnings and Precautions (5.3)].

Malignancies

In Study 1, two cases of basal cell carcinoma (0.4%) were reported in PONVORY-treated patients, compared to one case of basal cell carcinoma (0.2%) in patients receiving teriflunomide 14 mg, and a case of malignant melanoma was reported in a PONVORY-treated patient. An increased risk of cutaneous malignancies has been reported in association with other S1P receptor modulators, including PONVORY [see Warnings and Precautions (5.6)].

7 DRUG INTERACTIONS

7.1 Anti-Neoplastic, Immune-Modulating, or Immunosuppressive Therapies

PONVORY has not been studied in combination with anti-neoplastic, immune-modulating, or immunosuppressive therapies. Caution should be used during concomitant administration because of the risk of additive immune effects during such therapy and in the weeks following administration [see Warnings and Precautions (5.1)].

When switching from drugs with prolonged immune effects, the half-life and mode of action of these drugs must be considered in order to avoid unintended additive effects on the immune system [see Warnings and Precautions (5.10)].

Because of the characteristics and duration of alemtuzumab immune suppressive effects, initiating treatment with PONVORY after alemtuzumab is not recommended.

PONVORY can generally be started immediately after discontinuation of beta interferon or glatiramer acetate.

7.2 Anti-Arrhythmic Drugs, QT Prolonging Drugs, Drugs that may Decrease Heart Rate

PONVORY has not been studied in patients taking QT prolonging drugs.

Class Ia (e.g., quinidine, procainamide) and Class III (e.g., amiodarone, sotalol) anti-arrhythmic drugs have been associated with cases of Torsades de Pointes in patients with bradycardia. If treatment with PONVORY is considered, advice from a cardiologist should be sought.

Because of the potential additive effects on heart rate, treatment with PONVORY should generally not be initiated in patients who are concurrently treated with QT prolonging drugs with known arrhythmogenic properties, heart rate lowering calcium channel blockers (e.g., verapamil, diltiazem), or other drugs that may decrease heart rate (e.g., digoxin) [see Warnings and Precautions (5.2) and Drug Interactions (7.3)]. If treatment with PONVORY is considered, advice from a cardiologist should be sought.

7.3 Beta-Blockers

Caution should be applied when PONVORY is initiated in patients receiving treatment with a beta-blocker because of the additive effects on lowering heart rate; temporary interruption of the beta-blocker treatment may be needed prior to initiation of PONVORY [see Warnings and Precautions (5.2)]. Beta-blocker treatment can be initiated in patients receiving stable doses of PONVORY.

7.4 Vaccination

During, and for up to 1 to 2 weeks after discontinuation of, treatment with PONVORY, vaccinations may be less effective. The use of live attenuated vaccines may carry the risk of infection and should therefore be avoided during PONVORY treatment and for 1 to 2 weeks after discontinuation of treatment with PONVORY [see Warnings and Precautions (5.1)].

8 USE IN SPECIFIC POPULATIONS

8.1 Pregnancy

Risk Summary

There are no adequate and well-controlled studies of PONVORY in pregnant women. In animal studies, administration of ponesimod during pregnancy produced adverse effects on development, including embryo lethality and fetal malformations, in the absence of maternal toxicity. In rats and rabbits, visceral and skeletal malformations occurred at clinically relevant maternal ponesimod exposures (see Data). The receptor affected by ponesimod (sphingosine-1-phosphate receptor 1) has been demonstrated to have an important role in embryogenesis, including vascular and neural development.

In the US general population, the estimated background risk of major birth defects and miscarriage in clinically recognized pregnancies is 2%-4% and 15%-20%, respectively. The background risk of major birth defects and miscarriage for the indicated population is unknown.

Data

Animal Data

When ponesimod (0, 1, 10, or 40 mg/kg/day) was orally administered to pregnant rats during the period of organogenesis, increased incidences of fetal malformations primarily involving the limbs (syndactyly and ectrodactyly) and cardiovascular system (including ventricular septal defects) were observed at all but the lowest dose tested. A high incidence of embryofetal death was observed at the highest dose tested. Maternal toxicity was not observed, indicating a selective effect on the fetus. Plasma exposure (AUC) at the no-effect dose (1 mg/kg/day) for adverse effects on embryofetal development in rats was lower than that in humans at the recommended human dose (RHD) of 20 mg/day.

When ponesimod (0, 0.25, 1, or 4 mg/kg/day) was orally administered to pregnant rabbits during the period of organogenesis, an increase in post-implantation loss and fetal variations (visceral and skeletal) were noted at the highest dose tested. No maternal toxicity was observed. Plasma exposure at the no-effect dose (1 mg/kg/day) for adverse effects on embryofetal development in rabbits was lower than that in humans at the RHD. In a dose-range finding study in pregnant rabbits, oral administration of ponesimod (0, 6, 20, or 60 mg/kg/day) during organogenesis, an increase in embryofetal death and fetal limb malformation (brachydactyly) were observed at the lowest dose tested; at the higher doses, there were no live fetuses.

When ponesimod (5, 10, or 20 mg/kg) was orally administered to female rats throughout pregnancy and lactation, the offspring exhibited decreased survival, reduced body weight gain, and reduced fertility and reproductive performance (increases in pre- and post-implantation loss) at the highest dose tested, neurobehavioral impairment (increased locomotor activity) at the mid and high doses, and delayed sexual maturation at all doses tested. A no-effect dose for adverse effects on pre- and postnatal development in rats was not identified. Plasma exposure (AUC) in dams at the lowest dose tested was less than that in humans at the RHD.

8.2 Lactation

Risk Summary

There are no data on the presence of PONVORY in human milk, the effects on the breastfed infant, or the effects of the drug on milk production. When ponesimod was orally administered to female rats during pregnancy and lactation, ponesimod was detected in the plasma of the offspring, suggesting excretion of ponesimod in milk.

The developmental and health benefits of breastfeeding should be considered along with the mother’s clinical need for PONVORY and any potential adverse effects on the breastfed infant from PONVORY or from the underlying maternal condition.

8.3 Females and Males of Reproductive Potential

Contraception

Females

Before initiation of PONVORY treatment, women of childbearing potential should be counseled on the potential for a serious risk to the fetus and the need for effective contraception during treatment with PONVORY [see Use in Specific Populations (8.1)]. Since it takes approximately one week to eliminate ponesimod from the body after stopping treatment, the potential risk to the fetus may persist, and women should use effective contraception during this period [see Warnings and Precautions (5.7)].

8.4 Pediatric Use

Safety and effectiveness in pediatric patients have not been established.

Juvenile Animal Toxicity Data

Oral administration of ponesimod (0, 1, 10, 30, or 100 mg/kg/day) to young rats from postnatal day 28 to 91 resulted in lung histopathology (alveolar histiocytosis/edema) and decreased immune function (T-cell dependent antibody response) at the two highest doses tested. Decreased growth (body weight gain and/or long bone length) was observed at all but the low dose, and neurobehavioral impairment (increased locomotor activity) was observed at the highest dose tested. Decreased lymphocyte count and neurobehavioral impairment persisted at the end of a 4- week recovery period.

8.5 Geriatric Use

Clinical studies of PONVORY did not include patients 65 years of age and over to determine whether they respond differently from younger subjects. Use of PONVORY in elderly patients should be cautious, reflecting the greater frequency of decreased hepatic, renal, or cardiac function, and of concomitant disease or other drug therapy [see Clinical Pharmacology (12.3)].

8.6 Hepatic Impairment

No dosage adjustment is necessary in patients with mild hepatic impairment (Child-Pugh class A) [see Clinical Pharmacology (12.3)].

PONVORY is not recommended in patients with moderate or severe hepatic impairment (Child-Pugh class B and C, respectively), as the risk of adverse reactions may be greater [see Clinical Pharmacology (12.3)].

10 OVERDOSAGE

Symptoms and Signs

In patients with overdosage of PONVORY, especially upon initiation/reinitiation of treatment, it is important to observe for signs and symptoms of bradycardia as well as AV conduction blocks, which may include overnight monitoring. Regular measurements of pulse rate and blood pressure are required, and ECGs should be performed [see Warnings and Precautions (5.2, 5.5) and Clinical Pharmacology (12.2)].

Treatment

There is no specific antidote to ponesimod. Neither dialysis nor plasma exchange would result in meaningful removal of ponesimod from the body. The decrease in heart rate induced by PONVORY can be reversed by atropine.

In the event of overdose, PONVORY should be discontinued, and general supportive treatment given until clinical toxicity has been diminished or resolved. It is advisable to contact a poison control center to obtain the latest recommendations for the management of an overdose.

11 DESCRIPTION

PONVORY (ponesimod) is a sphingosine 1-phosphate receptor modulator.

The chemical name for ponesimod is (2Z,5Z)-5-[3-chloro-4-[(2R)-2,3- dihydroxypropoxy]benzylidene]-3-(2-methylphenyl)-2-(propylimino)-1,3-thiazolidin-4-one. It has one chiral center with absolute configuration of (R). Its molecular formula is C23H25ClN2O4S and its molecular weight is 460.97 g/mol. Ponesimod has the following structural formula:

Ponesimod is a white to light yellowish powder that is practically insoluble or insoluble in water.

PONVORY® (ponesimod) tablets are provided as 2 mg, 3 mg, 4 mg, 5 mg, 6 mg, 7 mg, 8 mg, 9 mg, 10 mg, and 20 mg film-coated tablets for oral administration.

Each tablet contains the following inactive ingredients: croscarmellose sodium, lactose monohydrate, magnesium stearate, microcrystalline cellulose, povidone K30, silica colloidal anhydrous, and sodium lauryl sulfate.

Each tablet coating contains ferrosoferric oxide (included in 4 mg, 5 mg, 8 mg, and 9 mg film-coated tablets), hydroxypropyl methylcellulose 2910, iron oxide red (included in 3 mg, 4 mg, 7 mg, 8 mg, 9 mg, and 10 mg film-coated tablets), iron oxide yellow (included in 3 mg, 5 mg, 7 mg, 9 mg, 10 mg, and 20 mg film-coated tablets), lactose monohydrate, polyethylene glycol 3350, titanium dioxide, and triacetin.

12 CLINICAL PHARMACOLOGY

12.1 Mechanism of Action

Ponesimod is a S1P receptor 1 modulator that binds with high affinity to S1P receptor 1.

Ponesimod blocks the capacity of lymphocytes to egress from lymph nodes, reducing the number of lymphocytes in peripheral blood. The mechanism by which ponesimod exerts therapeutic effects in MS is unknown, but may involve reduction of lymphocyte migration into the central nervous system.

12.2 Pharmacodynamics

Immune System

In healthy volunteers, PONVORY induces a dose-dependent reduction of the peripheral blood lymphocyte count from a single dose of 5 mg onwards, with the greatest reduction observed 6 hours post-dose, caused by reversible sequestration of lymphocytes in lymphoid tissues. After 7 daily doses of 20 mg, the greatest decrease in absolute mean lymphocyte count was to 26% of baseline (650 cells/µL), observed 6 hours after administration. Peripheral blood B cells [CD19+] and T cells [CD3+], T-helper [CD3+CD4+], and T-cytotoxic [CD3+CD8+] cell subsets are all affected, while NK cells are not. T-helper cells were more sensitive to the effects of ponesimod than T-cytotoxic cells.

PK/PD modeling indicates lymphocyte counts returned to the normal range in greater than 90% of healthy subjects within 1 to 2 weeks of stopping therapy. In Study 1, peripheral lymphocyte counts returned to the normal range within 2 weeks after discontinuation of PONVORY.

Heart Rate and Rhythm

PONVORY causes a transient dose-dependent reduction in heart rate and AV conduction delays upon treatment initiation [see Warnings and Precautions (5.2)]. The heart rate decreases plateaued at doses greater than or equal to 40 mg [2 times the recommended maintenance dosage], and bradyarrhythmic events (AV blocks) were detected at a higher incidence under PONVORY treatment, compared to placebo. This effect starts within the first hour of dosing and is maximal at 2-4 hours post-dose. Heart rate generally returns to pre-dose values by 4-5 hours post-dose on Day 1, and the effect diminishes with repeated administration, indicating tolerance.

The decrease in heart rate induced by ponesimod can be reversed by atropine.

Beta-Blockers

The negative chronotropic effect of coadministration of PONVORY and propranolol was evaluated in a dedicated pharmacodynamics safety study. The addition of PONVORY to propranolol at steady state has an additive effect on heart rate effect [see Drug Interactions (7.3)].

Cardiac Electrophysiology

In a thorough QT study, daily administration of ponesimod doses of 40 mg and 100 mg (respectively 2- and 5-fold the recommended maintenance dose) until steady-state conditions were achieved resulted in prolongation of Fridericia-corrected QT (QTcF) intervals, with the maximum mean (upper bound of 90% two-sided confidence interval) at 11.8 ms (40 mg) and 16.2 ms (100 mg). No subject had absolute QTcF greater than 480 ms or ΔQTcF greater than 90 ms for ponesimod treatment.

Pulmonary Function

Dose-dependent reductions in FEV1 and FVC were observed in PONVORY-treated subjects, and were greater than in subjects taking placebo [see Warnings and Precautions (5.3)]. These effects can be reversed with administration of a short acting beta2 agonist.

12.3 Pharmacokinetics

Following ponesimod oral dosing, Cmax and AUC increased approximately dose-proportionally in the dose-range studied (1-75 mg). Steady-state levels are approximately 2.0- to 2.6-fold greater than with a single dose, and are achieved following 3 days of administration of the maintenance dose of ponesimod.

The pharmacokinetics of ponesimod are similar in healthy subjects and patients with MS, with 25% inter-subject variability across studies.

Absorption

The time to reach maximum plasma concentration of ponesimod is 2-4 hours post-dose. The absolute oral bioavailability of a 10 mg dose is 84%.

Food Effect

Food does not have a clinically relevant effect on ponesimod pharmacokinetics; therefore, PONVORY may be taken with or without food.

Distribution

Following IV administration in healthy subjects, the steady-state volume of distribution of ponesimod is 160 L.

Ponesimod is highly bound to plasma proteins (>99%) and is mainly (78.5%) distributed in the plasma fraction of whole blood. Animal studies show that ponesimod readily crosses the blood-brain-barrier.

Metabolism

Ponesimod is extensively metabolized prior to excretion in humans, though unchanged ponesimod was the main circulating component in plasma. Two inactive circulating metabolites, M12 and M13, have also been identified in human plasma. M13 and M12 are respectively about 20% and 6% of total drug-related exposure. Both metabolites are inactive at S1P receptors at concentrations achieved with recommended doses of ponesimod.

Experiments with human liver preparations indicate that metabolism of ponesimod to M13 occurs primarily through a combination of non-Cytochrome P450 (CYP450) enzymatic activities. Multiple CYP450 (CYP2J2, CYP3A4, CYP3A5, CYP4F3A, and CYP4F12) and non-CYP450 enzymes catalyze the oxidation of ponesimod to M12. Ponesimod also undergoes direct glucuronidation (mainly UGT1A1 and UGT2B7).

Excretion

After a single IV administration, the total clearance of ponesimod is 3.8 L/hour. The elimination half-life after oral administration is approximately 33 hours.

Following a single oral administration of ^14C-ponesimod, 57% to 80% of the dose was recovered in feces (16% as unchanged ponesimod), and 10% to 18% in urine (no unchanged ponesimod).

Specific Populations

Renal Impairment

No dose adjustment is necessary in patients with renal impairment. In adult subjects with moderate or severe renal impairment (estimated creatinine clearance [CrCl], as determined by the Cockcroft-Gault, between 30-59 mL/min for moderate and <30 mL/min for severe), there were no significant changes in ponesimod Cmax and AUC, compared to subjects with normal renal function (CrCl>90 mL/min). The effect of dialysis on the PK of ponesimod has not been studied. Due to the high plasma protein binding (greater than 99%) of ponesimod, dialysis is not expected to alter the total and unbound ponesimod concentration, and no dose adjustments are anticipated based on these considerations.

Hepatic Impairment

In adult subjects with mild, moderate, or severe hepatic impairment (Child-Pugh class A, B and C, respectively), no change in ponesimod Cmax was observed, but ponesimod AUC0-∞ was increased by 1.3-, 2.0-, and 3.1-fold, respectively, compared to healthy subjects [see Use in Specific Populations (8.6)].

Age

Age (range: 17 to 65 years) was not identified to significantly influence the PK of ponesimod in population pharmacokinetics analyses. The effect of age (65 years of age and older) on the pharmacokinetics of ponesimod is unknown [see Use in Specific Populations (8.5)].

Gender

Gender has no clinically significant influence on ponesimod pharmacokinetics.

Race

No clinically relevant pharmacokinetic differences were observed between Japanese and Caucasian subjects.

Drug Interaction Studies

Beta-Blockers

In a drug-drug interaction study, the dose titration regimen of ponesimod [see Dosage and Administration (2.2)] was administered to subjects receiving propranolol (80 mg) once daily at steady state. No significant changes in pharmacokinetics of ponesimod or propranolol were observed. Compared to ponesimod alone, the combination of propranolol and the first dose of ponesimod (2 mg) led to a mean hourly heart rate decrease of 12.4 bpm (90% CI: -15.6 to -9.1). Compared to ponesimod alone, propranolol administered in combination with the first maintenance dose of ponesimod (20 mg) led to a 7.4 bpm (90% CI: -10.9 to -3.9) mean hourly heart rate decrease.

Effect of Other Drugs on Ponesimod

In vitro studies with human liver preparations indicate that metabolism of ponesimod occurs through multiple distinct enzyme systems, including multiple CYP450 (CYP2J2, CYP3A4, CYP3A5, CYP4F3A, and CYP4F12), UGT (mainly UGT1A1 and UGT2B7), and non-CYP450 oxidative enzymes, without major contribution by any single enzyme.

Ponesimod is not a substrate of P-gp, BCRP, OATP1B1, or OATP1B3 transporters. Drugs that are inhibitors of these transporters are unlikely to impact the PK of ponesimod.

Coadministration of carbamazepine 300 mg twice daily (a strong CYP3A4 and UGT1A1 inducer) at steady-state decreased ponesimod Cmax by 20% and AUC by 26%, which is not considered to be clinically significant.

Effect of Ponesimod on Other Drugs

In vitro investigations indicate that at the recommended dose of 20 mg once-daily, ponesimod and its metabolite M13 do not show any clinically relevant drug-drug interaction potential for CYP or UGT enzymes, or transporters.

Oral Contraceptives

Coadministration of ponesimod with an oral hormonal contraceptive (containing 1 mg norethisterone/norethindrone and 35 μg ethinyl estradiol) showed no clinically relevant pharmacokinetic interaction with ponesimod. Therefore, concomitant use of ponesimod is not expected to decrease the efficacy of hormonal contraceptives. No interaction studies have been performed with oral contraceptives containing other progestogens; however, an effect of ponesimod on their exposure is not expected.

13 NONCLINICAL TOXICOLOGY

13.1 Carcinogenesis, Mutagenesis, Impairment of Fertility

Carcinogenesis

Oral administration of ponesimod to mice (0, 50, 150, or 400 mg/kg/day in males and 30, 100, or 300 mg/kg/day in females) for up to 2 years resulted in incidences in hemangiosarcoma and combined hemangioma and hemangiosarcoma in males at all doses and at the highest dose tested in females. Plasma exposure (AUC) at the lowest dose tested in males (50 mg/kg/day) was approximately 5 times that in humans at the recommended human dose (RHD) of 20 mg.

Oral administration of ponesimod to rats (0, 3, 10, or 30 mg/kg/day in males and 0, 10, 30 or 100 mg/kg/day in females) for up to 2 years did not result in an increase in tumors. Plasma exposure at the highest dose tested in males (30 mg/kg/day) was approximately 4 times that in humans at the RHD of 20 mg.

Mutagenesis

Ponesimod was negative in a battery of in vitro (Ames, chromosomal aberration in mammalian cells) and in vivo (micronucleus in rat) assays.

Fertility

In separate studies, oral administration of ponesimod (0, 10, 30, or 100 mg/kg/day) to male and female rats prior to and throughout the mating period and continuing in females to Day 6 of gestation resulted in no effects on fertility. Plasma ponesimod exposures (AUC) at the highest dose tested were approximately 10 (males) and 30 (females) times that in humans at the RHD of 20 mg/day.

13.2 Animal Toxicology and/or Pharmacology

Increases in lung weight and histopathology (alveolar histiocytosis, edema) were observed in oral toxicity studies in mice, rats, and dogs. At the higher doses tested in short-term studies, alveolar histiocytosis was associated with lung edema, emphysema, or hyalinosis, and with bronchioloalveolar hyperplasia after cessation of dosing in rats and alveolar histiocytosis and hyalinosis in dogs. Effects tended to be absent or less severe after chronic treatment. These findings are considered secondary to increased vascular permeability caused by S1P1 receptor modulation. The NOAELs for lung findings in the 4-week oral toxicity studies in rats and dogs were associated with plasma exposures (AUC) similar or lower than that expected in humans at the RHD of 20 mg/day.

In dogs, coronary arterial lesions (thickening of the vessel wall, hyperplasia/hypertrophy of smooth muscles cells of the tunica media, subendocardial fibrosis) involving the papillary muscle of the left ventricle were observed in oral toxicity studies of 13 to 52 weeks in duration. At the NOAEL (2 mg/kg/day) for these findings, plasma exposures (AUC) were approximately 2 times that expected in humans at the RHD.

14 CLINICAL STUDIES

The efficacy of PONVORY was demonstrated in Study 1, a randomized, double-blind, parallel group, active-controlled superiority study in patients with relapsing forms of MS (NCT02425644). Patients were treated for 108 weeks. This study included patients who had an Expanded Disability Status Scale (EDSS) score of 0 to 5.5 at baseline, had experienced at least one relapse within the year prior, or two relapses within the prior 2 years, or who had at least one gadolinium-enhancing (Gd-enhancing) lesion on a brain MRI within the prior 6 months or at baseline. Patients with primary progressive MS were excluded.

Patients were randomized to receive either once daily PONVORY, beginning with a 14-day dose titration [see Dosage and Administration (2.2)] or teriflunomide 14 mg. Neurological evaluations were performed at baseline, every 3 months during the study, and at the time of a suspected relapse. Brain MRI scans were performed at baseline and at Weeks 60 and 108.

The primary endpoint was the annualized relapse rate (ARR) over the study period. Additional outcome measures included: 1) the number of new Gd-enhancing T1 lesions from baseline to Week 108, 2) the number of new or enlarging T2 lesions (without double-counting of lesions) from baseline to Week 108, and 3) the time to 3-month and 6-month confirmed disability progression. A confirmed disability progression was defined as an increase of at least 1.5 in EDSS for patients with a baseline EDSS score of 0, an increase of at least 1.0 in EDSS for patients with a baseline EDSS score of 1.0 to 5.0, or an increase of at least 0.5 in EDSS for patients with a baseline EDSS score at least 5.5, which was confirmed after 3 months and 6 months.

A total of 1133 patients were randomized to either PONVORY (N=567) or teriflunomide 14 mg (N=566); 86.4% of PONVORY-treated patients and 87.5% of teriflunomide 14 mg-treated patients completed the study as per protocol. At baseline, the mean age of patients was 37 years, 97% were White, and 65% were female. The mean disease duration was 7.6 years, the mean number of relapses in the previous year was 1.3, and the mean EDSS score was 2.6; 57% of patients had not received any prior non-steroid treatments for MS. At baseline, 42.6% of patients had one or more Gd-enhancing T1 lesions (mean 2.0) on their baseline MRI scan.

The ARR was statistically significantly lower in patients treated with PONVORY than in patients who received teriflunomide 14 mg. The number of Gd-enhancing T1 lesions and the number of new or enlarging T2 lesions were statistically significantly lower in patients treated with PONVORY than in patients who received teriflunomide 14 mg.

There was no statistically significant difference in the 3-month and 6-month confirmed disability progression outcomes between PONVORY- and teriflunomide 14 mg-treated patients over 108 weeks.

The efficacy results for Study 1 are presented in Table 4.

Table 4: Clinical and MRI Endpoints from Study 1

Endpoints | PONVORY 20 mg N=567 | Teriflunomide 14 mg N=566
Clinical Endpoints
Annualized Relapse Ratea | 0.202 | 0.290
Relative reduction | 30.5% (p=0.0003)
Percentage of patients without relapseb | 70.7% | 60.6%
Proportion of Patients with 3-month Confirmed Disability Progressionc | 10.8% | 13.2%
Hazard Ratiod | 0.83 (p=0.29)e
MRI Endpointsb,f
Mean number of new or enlarging T2 hyperintense lesions per year | 1.40 | 3.16
Relative reduction | 55.7% (p <.0001)
Mean number of T1 Gd-enhancing lesions per MRI | 0.18 | 0.43
Relative reduction | 58.5% (p <.0001)
All analyses are based on the full analysis set (FAS), which includes all randomized patients. N refers to the number of patients included in the FAS, per treatment group.
aDefined as confirmed relapses per year through the study period (Negative binomial regression model with stratification variables (EDSS ≤ 3.5 versus EDSS > 3.5; non-steroid treatment for MS within last 2 years prior to randomization [Yes/No]) and the number of relapses in the year prior to study entry (<=1, >=2) as covariates)
bOver the study period of approximately 108 weeks
cDisability progression defined as 1.5-point increase in EDSS for patients with a baseline EDSS score of 0, 1.0-point increase in EDSS for patients with a baseline EDSS score of 1.0 to 5.0, or 0.5-point increase in EDSS for patients with a baseline EDSS score at least 5.5 confirmed 3 months later. Proportion of patients with 3-month confirmed disability progression refers to Kaplan-Meier estimates at Week 108.
dDefined as time to 3 months confirmed disability progression through the study period (Stratified Cox proportional hazard model, p-value based on the stratified log rank test)
eNot statistically significant
fCumulative number of combined unique active lesions (CUALs), defined as new or enlarging T2 lesions or Gd-enhancing T1 lesions (without double counting), mean lesions per year were 1.41 on ponesimod 20 mg (N=539), and 3.16 on teriflunomide 14 mg (N=536), a relative reduction of 56% (p<0.0001).

A similar effect of PONVORY on the ARR and secondary MRI outcomes compared to teriflunomide 14 mg was observed in exploratory subgroups defined by age, gender, prior non-steroid therapy for MS, and baseline disease activity.

16 HOW SUPPLIED/STORAGE AND HANDLING

16.1 How Supplied

PONVORY® (ponesimod) tablet is available as round, biconvex, film-coated tablets supplied in the following dosage strengths and package configurations.

Starter Pack

Tablet Strength | Tablet Color | Tablet Size | Tablet Debossing | Pack Size | NDC Code
2 mg | White | 5.0 mm | "2" on one side and an arch on the other side. | Child Resistant Starter Pack (14 tablets) | NDC 43068-610-09
3 mg | Red | 5.0 mm | "3" on one side and an arch on the other side. | Child Resistant Starter Pack (14 tablets) | NDC 43068-610-09
4 mg | Purple | 5.0 mm | "4" on one side and an arch on the other side. | Child Resistant Starter Pack (14 tablets) | NDC 43068-610-09
5 mg | Green | 8.6 mm | "5" on one side and an arch and an "A" on the other side. | Child Resistant Starter Pack (14 tablets) | NDC 43068-610-09
6 mg | White | 8.6 mm | "6" on one side and an arch and an "A" on the other side. | Child Resistant Starter Pack (14 tablets) | NDC 43068-610-09
7 mg | Red | 8.6 mm | "7" on one side and an arch and an "A" on the other side. | Child Resistant Starter Pack (14 tablets) | NDC 43068-610-09
8 mg | Purple | 8.6 mm | "8" on one side and an arch and an "A" on the other side. | Child Resistant Starter Pack (14 tablets) | NDC 43068-610-09
9 mg | Brown | 8.6 mm | "9" on one side and an arch and an "A" on the other side. | Child Resistant Starter Pack (14 tablets) | NDC 43068-610-09
10 mg | Orange | 8.6 mm | "10" on one side and an arch and an "A" on the other side. | Child Resistant Starter Pack (14 tablets) | NDC 43068-610-09

Maintenance Dose Bottle

Tablet Strength | Tablet Color | Tablet Size | Tablet Debossing | Pack Size | NDC Code
20 mg | Yellow | 8.6 mm | "20" on one side and an arch and an "A" on the other side. | Bottle of 30 tablets with child-resistant closure. Each bottle contains a desiccant sachet. | NDC 43068-620-01

16.2 Storage and Handling

Starter Pack

Store at 20°C to 25°C (68°F to 77°F); excursions permitted from 15°C to 30°C (59°F to 86°F) [see
USP Controlled Room Temperature].

Store in the original package.

Maintenance Dose Bottle

Store at 20°C to 25°C (68°F to 77°F); excursions permitted from 15°C to 30°C (59°F to 86°F) [see
USP Controlled Room Temperature].

Store in the original package. Do not discard desiccant. Protect from moisture.

Keep out of reach of children.

17 PATIENT COUNSELING INFORMATION

Advise the patient to read the FDA-approved patient labeling (Medication Guide).

Administration

Tell patients not to discontinue PONVORY without first discussing this with the prescribing healthcare provider. Advise patients to contact their healthcare provider if they accidently take more PONVORY than prescribed.

Instruct patients to administer tablets whole.

Risk of Infections

Inform patients that they may have an increased risk of infections, some of which could be life-threatening, when taking PONVORY and for 1 to 2 weeks after stopping it, and that they should contact their healthcare provider if they develop symptoms of infection [see Warnings and Precautions (5.1)]. Advise patients that the use of some vaccines containing live virus (live attenuated vaccines) should be avoided during treatment with PONVORY, and PONVORY should be paused 1 to 2 weeks prior and until 4 weeks after a planned vaccination. Recommend that patients postpone treatment with PONVORY for at least 1 month after VZV vaccination. Inform patients that prior or concomitant use of drugs that suppress the immune system may increase the risk of infection.

Inform patients that cases of progressive multifocal leukoencephalopathy (PML) have occurred in patients treated with S1P receptor modulators. Inform the patient that PML is characterized by a progression of deficits and usually leads to death or severe disability over weeks or months. Instruct the patient of the importance of contacting their doctor if they develop any symptoms suggestive of PML. Inform the patient that typical symptoms associated with PML are diverse, progress over days to weeks, and include progressive weakness on one side of the body or clumsiness of limbs, disturbance of vision, and changes in thinking, memory, and orientation leading to confusion and personality changes [see Warnings and Precautions (5.1)].

Cardiac Effects

Advise patients that initiation of PONVORY treatment results in transient decrease in heart rate [see Warnings and Precautions (5.2)]. Inform patients that to reduce this effect, dose titration is required. Advise patients that dose titration is also required if 4 or more consecutive daily doses are missed during treatment initiation or maintenance treatment [see Dosage and Administration (2.2, 2.4) and Warnings and Precautions (5.2)]. Inform certain patients with certain preexisting cardiac conditions that they will need to be observed in the doctor's office or other facility for at least 4 hours after the first dose and after reinitiation if treatment is interrupted or discontinued for certain periods [see Dosage and Administration (2.3)].

Respiratory Effects

Advise patients that they should contact their healthcare provider if they experience new onset or worsening of dyspnea [see Warnings and Precautions (5.3)].

Liver Injury

Inform patients that PONVORY may increase liver enzymes. Advise patient that they should contact their healthcare provider if they experience any unexplained nausea, vomiting, abdominal pain, fatigue, anorexia, or jaundice and/or dark urine during treatment [see Warnings and Precautions (5.4)].

Cutaneous Malignancies

Inform patients that the risk of basal cell carcinoma is increased with the use of PONVORY and that cases of melanoma and squamous cell carcinoma have been reported. Advise patients that any suspicious skin lesions should be promptly evaluated. Advise patients to limit exposure to sunlight and ultraviolet light by wearing protective clothing and using a sunscreen with high protection factor [see Warnings and Precautions (5.6)].

Pregnancy and Fetal Risk

Inform patients that, based on animal studies, PONVORY may cause fetal harm. Discuss with women of childbearing age whether they are pregnant, might be pregnant, or are trying to become pregnant. Advise women of childbearing potential of the need for effective contraception during treatment with PONVORY and for one week after stopping PONVORY. Advise a female patient to immediately inform her healthcare provider if she is pregnant or planning to become pregnant [see Warnings and Precautions (5.7)].

Macular Edema

Advise patients that PONVORY may cause macular edema, and that they should obtain an eye exam near the start of treatment with PONVORY, have their eyes monitored periodically by an eye care professional while receiving therapy, and contact their healthcare provider if they experience any changes in their vision while taking PONVORY [see Warnings and Precautions (5.8)]. Inform patients with diabetes mellitus or a history of uveitis that their risk of macular edema is increased.

Posterior Reversible Encephalopathy Syndrome

Advise patients to immediately report to their healthcare provider any symptoms involving sudden onset of severe headache, altered mental status, visual disturbances, or seizure. Inform patients that delayed treatment could lead to permanent neurological sequelae [see Warnings and Precautions (5.9)].

Severe Increase in Disability After Stopping PONVORY

Inform patients that severe increase in disability has been reported after discontinuation of another S1P receptor modulator like PONVORY. Advise patients to contact their healthcare provider if they develop worsening symptoms of MS following discontinuation of PONVORY [see Warnings and Precautions (5.11)].

Immune System Effects After Stopping PONVORY

Advise patients that PONVORY continues to have effects, such as lowering effects on peripheral lymphocyte count, for 1 to 2 weeks after the last dose [see Warnings and Precautions (5.12)].

Active ingredient made in Austria.

Distributed by:
Vanda Pharmaceuticals, Inc.
Washington, D.C. 20037, USA

© 2024 Vanda Pharmaceuticals, Inc.

MEDICATION GUIDE
PONVORY ®(pon-VOR-ee)
(ponesimod)
tablets, for oral use

What is the most important information I should know about PONVORY?

PONVORY may cause serious side effects, including:

1. Infections. PONVORY can increase your risk of serious infections that can be life-threatening and cause death. PONVORY lowers the number of white blood cells (lymphocytes) in your blood. This will usually go back to normal within 1 to 2 weeks of stopping treatment. Your healthcare provider should review a recent blood test of your white blood cells before you start taking PONVORY.
  Call your healthcare provider right away if you have any of these symptoms of an infection during treatment with PONVORY and for 1 to 2 weeks after your last dose of PONVORY:
  - fever
  - tiredness
  - body aches
  - chills
  - nausea
  - vomiting
  - headache with fever, neck stiffness, sensitivity to light, nausea, or confusion (these may be symptoms of meningitis, an infection of the lining around your brain and spine)
  Your healthcare provider may delay starting or may stop your PONVORY treatment if you have an infection.
2. Slow heart rate (bradycardia or bradyarrhythmia) when you start taking PONVORY. PONVORY can cause your heart rate to slow down, especially after you take your first dose. You should have a test to check the electrical activity of your heart called an electrocardiogram (ECG) before you take your first dose of PONVORY.
  Only start your treatment with PONVORY using the Starter Pack.You must use the PONVORY Starter Pack to slowly increase the dose over a 14-day period to help reduce the effect of slowing of your heart rate. It is important to follow the recommended dosing instructions. See " How should I take PONVORY?"
  Call your healthcare provider if you experience the following symptoms of slow heart rate:
  - dizziness
  - shortness of breath
  - lightheadedness
  - confusion
  - feeling like your heart is beating slowly or skipping beats
  - chest pain
  - tiredness

Follow directions from your healthcare provider when starting PONVORY and when you miss a dose. See " How should I take PONVORY?"

See "What are possible side effects of PONVORY?" for more information about side effects.

What is PONVORY?

- PONVORY is a prescription medicine that is used to treat relapsing forms of multiple sclerosis, to include clinically isolated syndrome, relapsing-remitting disease, and active secondary progressive disease, in adults.
- It is not known if PONVORY is safe and effective in children.

Do not take PONVORY if you:

- have had a heart attack, chest pain called unstable angina, stroke or mini-stroke (transient ischemic attack or TIA), or certain types of heart failure in the last 6 months.
- have certain types of heart block or irregular or abnormal heartbeat (arrhythmia), unless you have a pacemaker.

Talk to your healthcare provider before taking PONVORY if you have any of these conditions, or do not know if you have any of these conditions.

Before you take PONVORY, tell your healthcare provider about all of your medical conditions, including if you:

- have a fever or infection, or you are unable to fight infections due to a disease or taking medicines that weaken your immune system.
- have had chicken pox or have received the vaccine for chicken pox. Your healthcare provider may do a blood test for chicken pox virus. You may need to get the full course of vaccine for chicken pox and then wait 1 month before you start taking PONVORY.
- have slow heart rate.
- have an irregular or abnormal heartbeat (arrhythmia).
- have a history of stroke.
- have heart problems, including a heart attack or chest pain.
- have breathing problems, including during your sleep (sleep apnea).
- have liver problems.
- have high blood pressure.
- had or now have any types of skin cancer, including basal cell carcinoma (BCC), melanoma, or squamous cell carcinoma (SCC).
- have eye problems, especially an inflammation of the eye called uveitis.
- have diabetes.
- are pregnant or plan to become pregnant. PONVORY may harm your unborn baby. Talk with your healthcare provider if you are pregnant or plan to become pregnant. If you are a woman who can become pregnant, you should use effective birth control during your treatment with PONVORY and for 1 week after you stop taking PONVORY. Talk to your healthcare provider about what method of birth control is right for you during this time. Tell your healthcare provider right away if you do become pregnant while taking PONVORY or within 1 week after you stop taking PONVORY.
- are breastfeeding or plan to breastfeed. It is not known if PONVORY passes into your breast milk. Talk to your healthcare provider about the best way to feed your baby if you take PONVORY.

Tell your healthcare provider about all the medicines you take, including prescription medicines, over-the-counter medicines, vitamins, and herbal supplements.
Using PONVORY and other medicines together may affect each other causing serious side effects.

Especially tell your healthcare provider if you take or have taken:

- medicines to control your heart rhythm (antiarrhythmics), or blood pressure (antihypertensives), or heart beat (such as calcium channel blockers or beta-blockers).
- medicines that affect your immune system, such as alemtuzumab.
- You should not receive live vaccines during treatment with PONVORY, for at least 1 month before taking PONVORY, and for 1 to 2 weeks after you stop taking PONVORY. If you receive a live vaccine, you may get the infection the vaccine was meant to prevent. Vaccines may not work as well when given during treatment with PONVORY.

Talk with your healthcare provider if you are not sure if you take any of these medicines.
Know the medicines you take. Keep a list of your medicines with you to show your healthcare provider and pharmacist when you get a new medicine.

How should I take PONVORY?
You will receive a 14-day starter pack. You must start PONVORY by slowly increasing doses over the first two weeks. Follow the dose schedule in the table below. This may reduce the risk of slowing of the heart rate.

Starter Pack Day

Daily Dose

Day 1

2 mg tablet 1 time a day

Day 2

2 mg tablet 1 time a day

Day 3

3 mg tablet 1 time a day

Day 4

3 mg tablet 1 time a day

Day 5

4 mg tablet 1 time a day

Day 6

4 mg tablet 1 time a day

Day 7

5 mg tablet 1 time a day

Day 8

6 mg tablet 1 time a day

Day 9

7 mg tablet 1 time a day

Day 10

8 mg tablet 1 time a day

Day 11

9 mg tablet 1 time a day

Day 12

10 mg tablet 1 time a day

Day 13

10 mg tablet 1 time a day

Day 14

10 mg tablet 1 time a day

Maintenance

Daily Dose

Day 15 and thereafter

20 mg tablet 1 time a day

- Take PONVORY exactly as your healthcare provider tells you to take it.
- Take PONVORY 1 time each day.
- Swallow PONVORY tablets whole.
- Take PONVORY with or without food.
- Do not stop taking PONVORY without talking with your healthcare provider first.
- Do not skip a dose.
- Start taking PONVORY with a 14-day starter pack.
- If you miss taking 1, 2, or 3 tablets in a row of PONVORY in the 14-day starter pack, continue treatment by taking the first dose you missed. Take 1 tablet as soon as you remember. Then, take 1 tablet a day to continue with the starter pack dose as planned.
- If you miss taking 1, 2, or 3 tablets in a row of PONVORY while taking the 20 mg maintenance dose, continue treatment with the 20 mg maintenance dose.
- If you miss taking 4 or more tablets in a row of PONVORY, while taking the 14-day starter pack or the 20 mg maintenance dose, you need to restart treatment with a new 14-day starter pack. Call your healthcare provider if you miss 4 or more doses of PONVORY. Do not restart PONVORY after stopping it for 4 or more days in a row without talking to your healthcare provider. If you have certain heart conditions, you may need to be monitored by your healthcare provider for at least 4 hours when you take your next dose.
- Write down the date you start taking PONVORY so you will know if you miss 4 or more doses in a row.

What are the possible side effects of PONVORY?
PONVORY may cause serious side effects, including:

- See " What is the most important information I should know about PONVORY?"
- breathing problems. Some people who take PONVORY have shortness of breath. Call your healthcare provider right away if you have new or worsening breathing problems.
- liver problems. PONVORY may cause liver problems. Your healthcare provider should do blood tests to check your liver before you start taking PONVORY. Call your healthcare provider right away if you have any of the following symptoms of liver problems:

- unexplained nausea
- vomiting
- stomach (abdominal) pain
- tiredness

- loss of appetite
- yellowing of the whites of your eyes or skin
- dark urine

- increased blood pressure. Your healthcare provider should check your blood pressure during treatment with PONVORY.
- types of skin cancer, including basal cell carcinoma, melanoma, and squamous cell carcinoma. Tell your healthcare provider if you have any changes in the appearance of your skin, including changes in a mole, a new darkened area on your skin, a sore that does not heal, or growths on your skin, such as a bump that may be shiny, pearly white, skin-colored, or pink. Your doctor should check your skin for any changes at the start of and during treatment with PONVORY. Limit the amount of time you spend in sunlight and ultraviolet (UV) light. Wear protective clothing and use a sunscreen with a high sun protection factor.
- a problem with your vision called macular edema. Macular edema can cause some of the same vision symptoms as a multiple sclerosis (MS) attack (optic neuritis). You may not notice any symptoms with macular edema. Your healthcare provider should test your vision around the time you start taking PONVORY, periodically while you continue taking PONVORY, and any time you notice vision changes during treatment with PONVORY. Your risk of macular edema is higher if you have diabetes or have had an inflammation of your eye called uveitis.

Call your healthcare provider right away if you have any of the following symptoms:

- blurriness or shadows in the center of your vision
- a blind spot in the center of your vision

- sensitivity to light
- unusually colored (tinted) vision

- swelling and narrowing of the blood vessels in your brain. A condition called Posterior Reversible Encephalopathy Syndrome (PRES) has happened with drugs in the same class. Symptoms of PRES usually get better when you stop taking PONVORY. However, if left untreated, it may lead to a stroke. Call your healthcare provider right away if you have any of the following symptoms:

- sudden severe headache
- sudden confusion

- sudden loss of vision or other changes in your vision
- seizure

- severe worsening of multiple sclerosis after stopping PONVORY. When PONVORY is stopped, symptoms of MS may return and become worse compared to before or during treatment. Always talk to your healthcare provider before you stop taking PONVORY for any reason. Tell your healthcare provider if you have worsening symptoms of MS after stopping PONVORY.

The most common side effects of PONVORY include:

- upper respiratory tract infections
- elevated liver enzymes (abnormal liver tests)
- high blood pressure

These are not all of the possible side effects of PONVORY.
For more information, ask your healthcare provider or pharmacist.
Call your healthcare provider for medical advice about side effects. You may report side effects to FDA at 1-800-FDA-1088.

How should I store PONVORY?

- Store PONVORY at room temperature between 68°F to 77°F (20°C to 25°C).
- Store PONVORY in the original package.
- The bottle of PONVORY contains a desiccant sachet to help keep your medicine dry (protect it from moisture). Do not throw away (discard) the desiccant.

Keep PONVORY and all medicines out of the reach of children.

General information about the safe and effective use of PONVORY.

Medicines are sometimes prescribed for purposes other than those listed in a Medication Guide. Do not use PONVORY for conditions for which it was not prescribed. Do not give PONVORY to other people, even if they have the same symptoms that you have. It may harm them.

You can ask your healthcare provider or pharmacist for information about PONVORY that is written for health professionals.

What are the ingredients in PONVORY?

Active ingredient: ponesimod

Inactive ingredients:

Tablet core: croscarmellose sodium, lactose monohydrate, magnesium stearate, microcrystalline cellulose, povidone K30, silica colloidal anhydrous, and sodium lauryl sulfate.

Tablet coating: ferrosoferric oxide (included in 4 mg, 5 mg, 8 mg and 9 mg film-coated tablets), hydroxypropyl methylcellulose 2910, iron oxide red (included in 3 mg, 4 mg, 7 mg, 8 mg, 9 mg and 10 mg film-coated tablets), iron oxide yellow (included in 3 mg, 5 mg, 7 mg, 9 mg, 10 mg and 20 mg film-coated tablets), lactose monohydrate, polyethylene glycol 3350, titanium dioxide, and triacetin.

Manufactured for: Vanda Pharmaceuticals, Inc., Washington, D.C. 20037, USA
© 2024 Vanda Pharmaceuticals, Inc.
For more information, go to www.ponvoryus.com or call 833-933-9331.

This Medication Guide has been approved by the U.S. Food and Drug Administration.

Revised: 06/2024